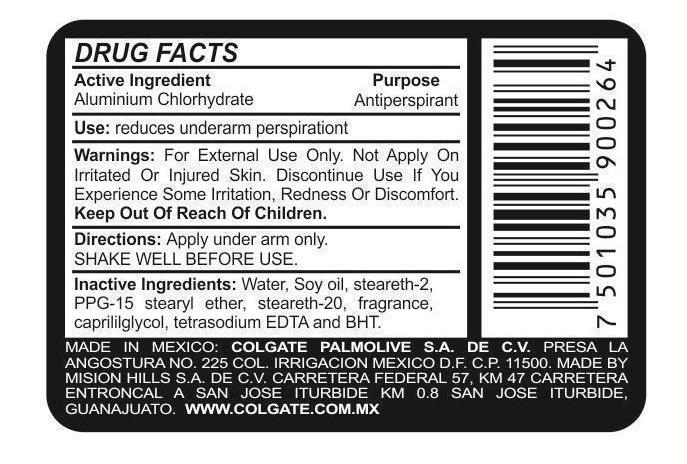 DRUG LABEL: STEFANO ROYAL
NDC: 69772-050 | Form: LIQUID
Manufacturer: TERESA CECENA DBA GENESIS
Category: otc | Type: HUMAN OTC DRUG LABEL
Date: 20160129

ACTIVE INGREDIENTS: ALUMINUM CHLOROHYDRATE 25 g/50 mL
INACTIVE INGREDIENTS: EDETATE SODIUM; BUTYLATED HYDROXYTOLUENE; WATER; STEARETH-2; PPG-15 STEARYL ETHER; ISOSTEARETH-20; CAPRYLYL GLYCOL

ACTIVE INGREDIENT

Aluminium chlorhydrate

PURPOSE:

Antiperspirant

KEEP OUT THE REACH OF CHILDREN

USE:

Reduces underarm persperation

FOR EXTERNAL USE ONLY

WARNINGS AND PRECAUTIONS

DIRECTION

APPLY UNDER ARM ONLY

SHAKE WELL BEFORE USE

DO NOT APPLY ON IRRITATED OR INJURED SKIN. DISCONTINUE USE IF YOU EXPERIENCE SOME IRRITATION, REDNESS OR DSCOMFORT

INACTIVE INGREDIENT

WATER, SOY OIL, STEARTH2, PPG-15 STEARYL ETHER, STEARETH-20,FRAGANCE, CAPRYLYGLYCOL, TETRASODIUM, AND BHT

INDICATIONS AND USAGE

APPLY UNDER ARM

WARNINGS

DO NOT APPLY ON IRRITATED OR INJURED SKIN, DISCONTINUE USE IF YOU EXPERIENCE SOME IRRITION, REDNESS OR DISCOMFORT